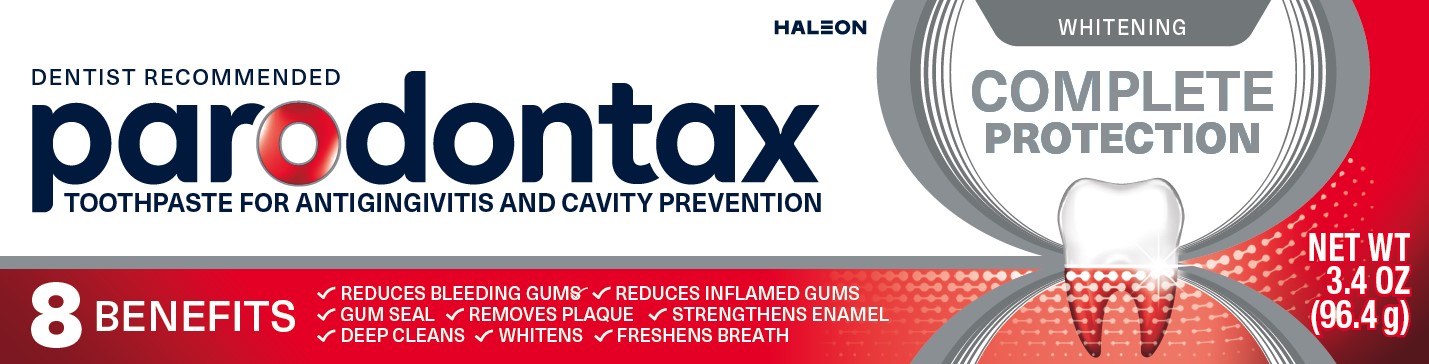 DRUG LABEL: parodontax
NDC: 0135-0634 | Form: PASTE
Manufacturer: Haleon US Holdings LLC
Category: otc | Type: HUMAN OTC DRUG LABEL
Date: 20251222

ACTIVE INGREDIENTS: STANNOUS FLUORIDE 1.10 mg/1 g
INACTIVE INGREDIENTS: GLYCERIN; POLYETHYLENE GLYCOL 400; HYDRATED SILICA; SODIUM TRIPOLYPHOSPHATE ANHYDROUS; SODIUM LAURYL SULFATE; TITANIUM DIOXIDE; POLYACRYLIC ACID (250000 MW); COCAMIDOPROPYL BETAINE; SACCHARIN SODIUM

Drug Facts

Active ingredient

Stannous fluoride 0.454% (0.15% w/v fluoride ion)

Purposes

Anticavity, Antigingivitis

Uses

- aids in the prevention of dental cavities.
- helps control bleeding gums.
- helps interfere with harmful effects of plaque associated with gingivitis.

Warnings

Stop use and ask a dentist if

- gingivitis, bleeding, or redness persists for more than 2 weeks.
- you have painful or swollen gums, pus from the gum line, loose teeth, or increasing spacing between the teeth. These may be signs or symptoms of periodontitis, a serious form of gum disease.

Keep out of reach of children under 6 years of age.

If more than used for brushing is accidentally swallowed, get medical help or contact a Poison Control Center right away.

Directions

- adults and children 2 years of age and older:
  - brush teeth thoroughly, preferably after each meal at least twice a day, or as directed by a dentist or doctor. Minimize swallowing.
  - to minimize swallowing for children under 6 years of age, use a pea-sized amount and supervise brushing and rinsing until good habits are established.
- children under 2 years of age: Consult a dentist or doctor.

Other Information

- products containing stannous fluoride may produce surface staining of the teeth. Adequate toothbrushing may prevent these stains which are not harmful or permanent and may be removed by your dentist.
- this product is specially formulated to help prevent staining.
- do not store above 25ºC (77ºF)

Inactive ingredients

glycerin, PEG-8, hydrated silica, pentasodium triphosphate, flavor, sodium lauryl sulfate, titanium dioxide, polyacrylic acid, cocamidopropyl betaine, sodium saccharin

Questions or comments?

1-866-844-2797

Additional Information

ALWAYS FOLLOW THE LABEL

parodontax COMPLETE PROTECTION

Bleeding, redness, and swelling can be signs of unhealthy gums, eventually weakening the foundation of your teeth.

parodontax Complete Protection builds on the gum health expertise behind our dentist recommended daily fluoride toothpaste – providing 8 benefits designed for healthy gums and strong teeth.

With a fresh minty flavor to enjoy every day.

8 BENEFITS FOR HEALTHY GUMS & STRONG TEETH

Gently whitens

Deep cleans

Helps prevent bleeding gums

Effectively removes plaque

Strengthens and protects enamel

Freshens breath

Works to keep the seal between gums and teeth tight

Reduces red and inflamed gums

Principal Display Panel

DENTIST RECOMMENDED

parodontax

TOOTHPASTE FOR ANTIGINGIVITIS AND CAVITY PREVENTION

WHITENING

COMPLETE PROTECTION

8 BENEFITS

✓ REDUCES BLEEDING GUMS
✓ REDUCES INFLAMED GUMS
✓ GUM SEAL
✓ REMOVES PLAQUE
✓ STRENGTHENS ENAMEL
✓ DEEP CLEANS
✓ WHITENS
✓ FRESHENS BREATH

NET WT 3.4 OZ (96.4 g)